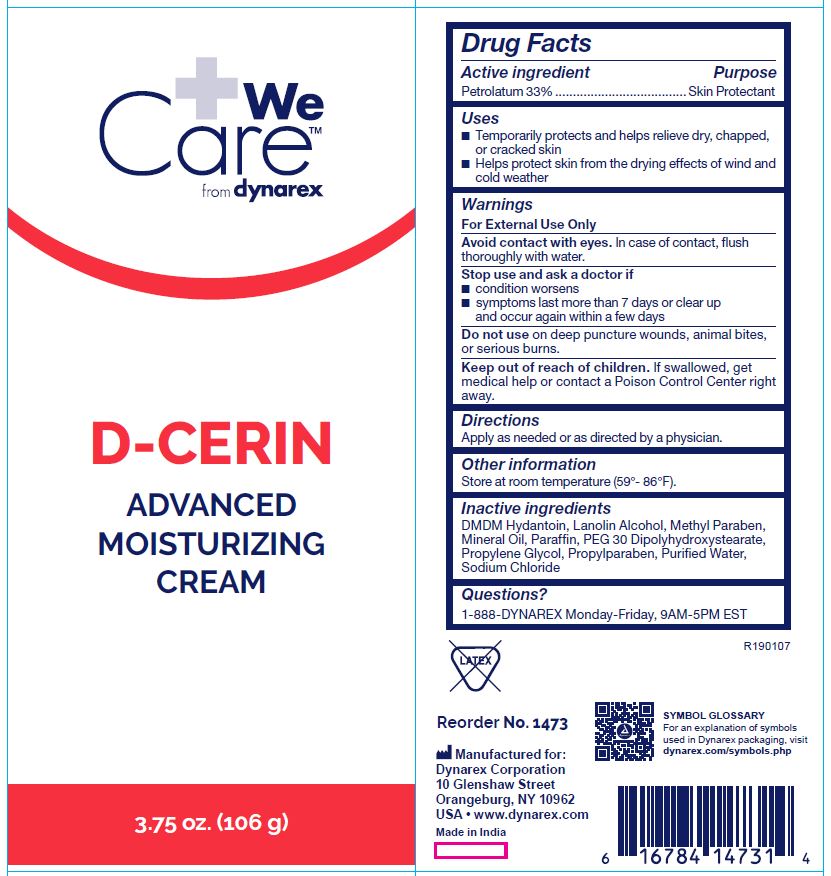 DRUG LABEL: D-Cerin
NDC: 67777-147 | Form: CREAM
Manufacturer: Dynarex Corporation
Category: otc | Type: HUMAN OTC DRUG LABEL
Date: 20241119

ACTIVE INGREDIENTS: PETROLATUM 33 g/100 g
INACTIVE INGREDIENTS: PROPYLPARABEN; SODIUM CHLORIDE; WATER; PARAFFIN; PEG-30 DIPOLYHYDROXYSTEARATE; LANOLIN ALCOHOLS; DMDM HYDANTOIN; MINERAL OIL; METHYLPARABEN; PROPYLENE GLYCOL

1473 D-Cerin, NDC 67777-147-30

Active ingredient

Petrolatum 33%

Purpose

Skin Protectant

Use(s)

• Temporarily protects and helps relieve dry, chapped, or cracked skin

• Helps protect skin from the drying effects of wind and cold weather

Warnings

For External Use Only

Avoid contact with eyes.

In case of contact, flush thoroughly with water.

Stop use and ask a doctor if

- Conditions worsens
- Symptoms last more than 7 days or clear up and occur again within a few days

Do not use

• On deep puncture wounds • Animal bites • Serious burns.

Keep out of reach of children

If swallowed, get medical help or contact a Poison Control Center (1-800-222-1222) right away.

Directions

Apply as needed or as directed by a physician.

Other information

• Store at room temperature 15º-30ºC (59° - 86°F)

• Tamper evident. Do not use if seal is damaged.

Inactive Ingredients

DMDM Hydantoin, Lanolin Alcohol, Methyl Paraben, Mineral Oil, Paraffin, PEG 30 Dipolyhydroxystearate, Propylene Glycol, Propylparaben, Purified Water, Sodium Chloride

Questions?

1-888-DYNAREX Monday-Friday, 9AM-5PM EST